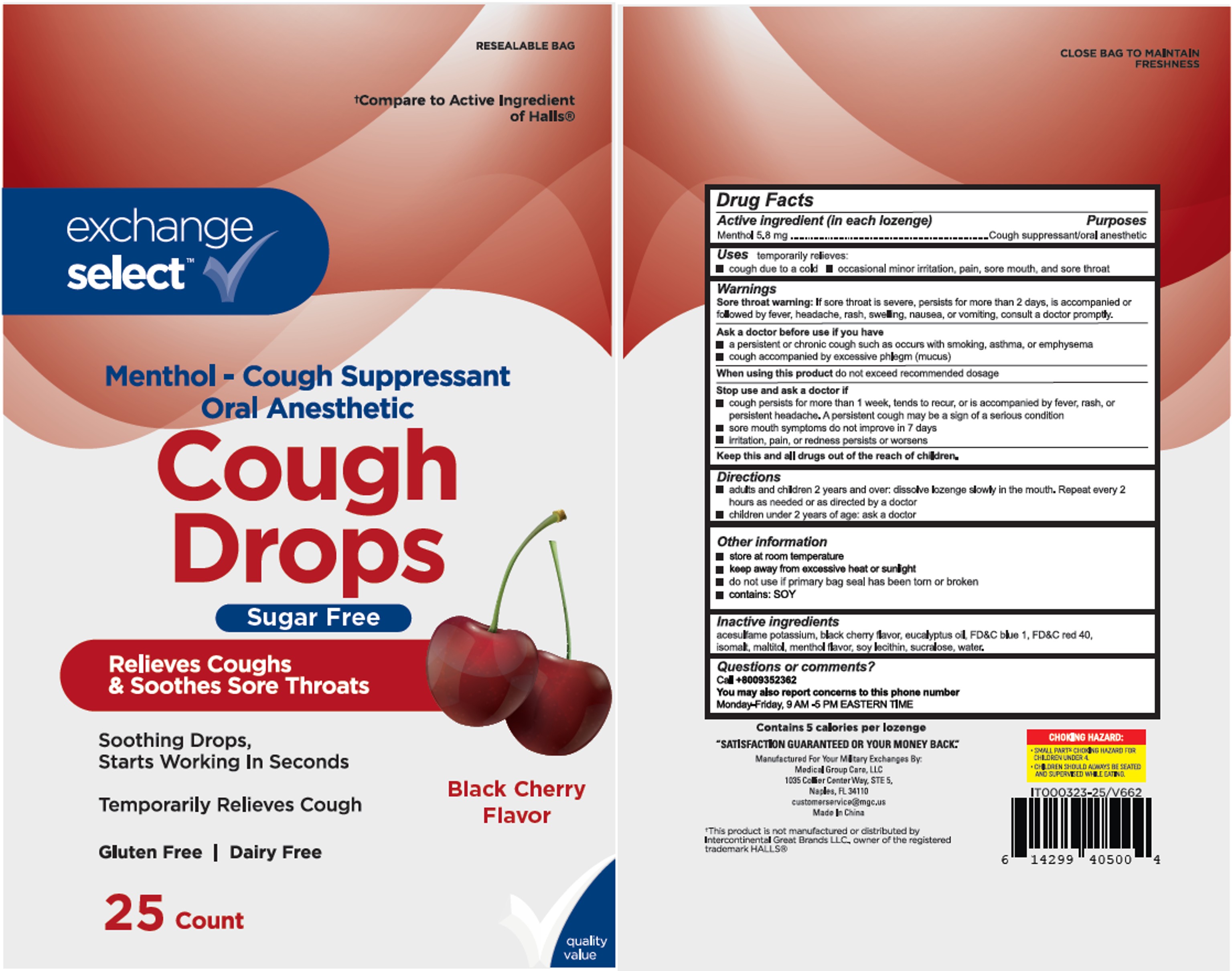 DRUG LABEL: Exchange Select Cough Drop
NDC: 55301-582 | Form: LOZENGE
Manufacturer: Army & Air Force Exchange Service
Category: otc | Type: HUMAN OTC DRUG LABEL
Date: 20250620

ACTIVE INGREDIENTS: MENTHOL 5.8 mg/1 1
INACTIVE INGREDIENTS: SUCRALOSE; MALTITOL; LECITHIN, SOYBEAN; ISOMALT; EUCALYPTUS OIL; FD&C BLUE NO. 1; FD&C RED NO. 40; WATER; ACESULFAME POTASSIUM

Xiamen AAFES BC SF

Active Ingredient(s)

Menthol 5.8 mg

Purpose

Purposes cough suppressant, oral anesthetic

Use

temporary relieves: ■ cough due to cold ■ occasional minor irritation, pain, sore mouth, and sore throat

Warnings

Sore throat warning: If sore throat is severe, persists for more than 2 days, is accompanied or follow headache, rash, swelling, nausea, or vomiting, consult a doctor promptly.

Ask a doctor before use if you have: ■ persistent or chronic cough such as occurs with smoking, asthma, or emphysema ■ cough accompanied by excessive phlegm (mucus).

When using this product do not exceed recommended dosage

Stop use and ask a doctor if ■ cough persists for more than 1 week, tends to recur, or is accompained by fever, rash, or persistent headache. These could be signs of a serius condition. ■ sore mouth does not improve in 7 days ■ irritation, pain, or redness persists or worsens.

Keep out of reach of children.

Directions

■ adults and children 2 years and over: dissolve lozenge slowly in the mouth. Repeat every 2 hours as needed.

■ children under 2 years: ask a doctor.

Other information

■ 5 calories per drop ■ store at room temperature ■ keep away from excessive heat or sunlight ■ do not use if primary bag seal has been torn or broken ■ contains: SOY.

Inactive ingredients

Acesulfame potassium, black cherry flavor, eucalyptus oil, FD&C blue 1, FD&C red 40, isomalt, maltitol, menthol flavor, soy lecithin, sucralose, water

QUESTIONS

call +8009352362. You may also report concerns to this phone number. Monday - Friday, 9 AM to 5 PM EASTERN TIME